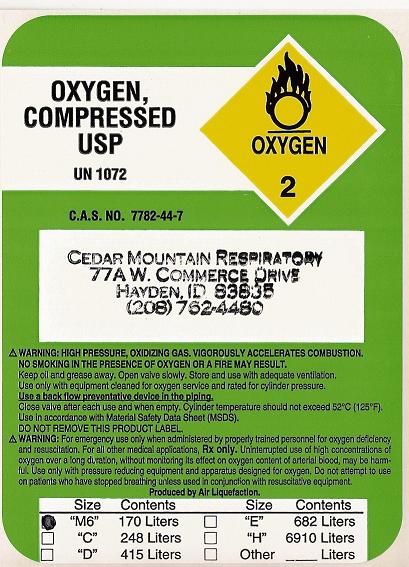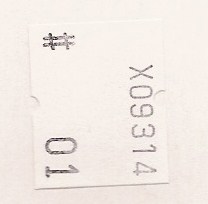 DRUG LABEL: Oxygen
NDC: 23916-1234 | Form: GAS
Manufacturer: Cedar Mountain Respiratory, Inc. 
Category: prescription | Type: HUMAN PRESCRIPTION DRUG LABEL
Date: 20091113

ACTIVE INGREDIENTS: Oxygen 99 L/100 L

Oxygen